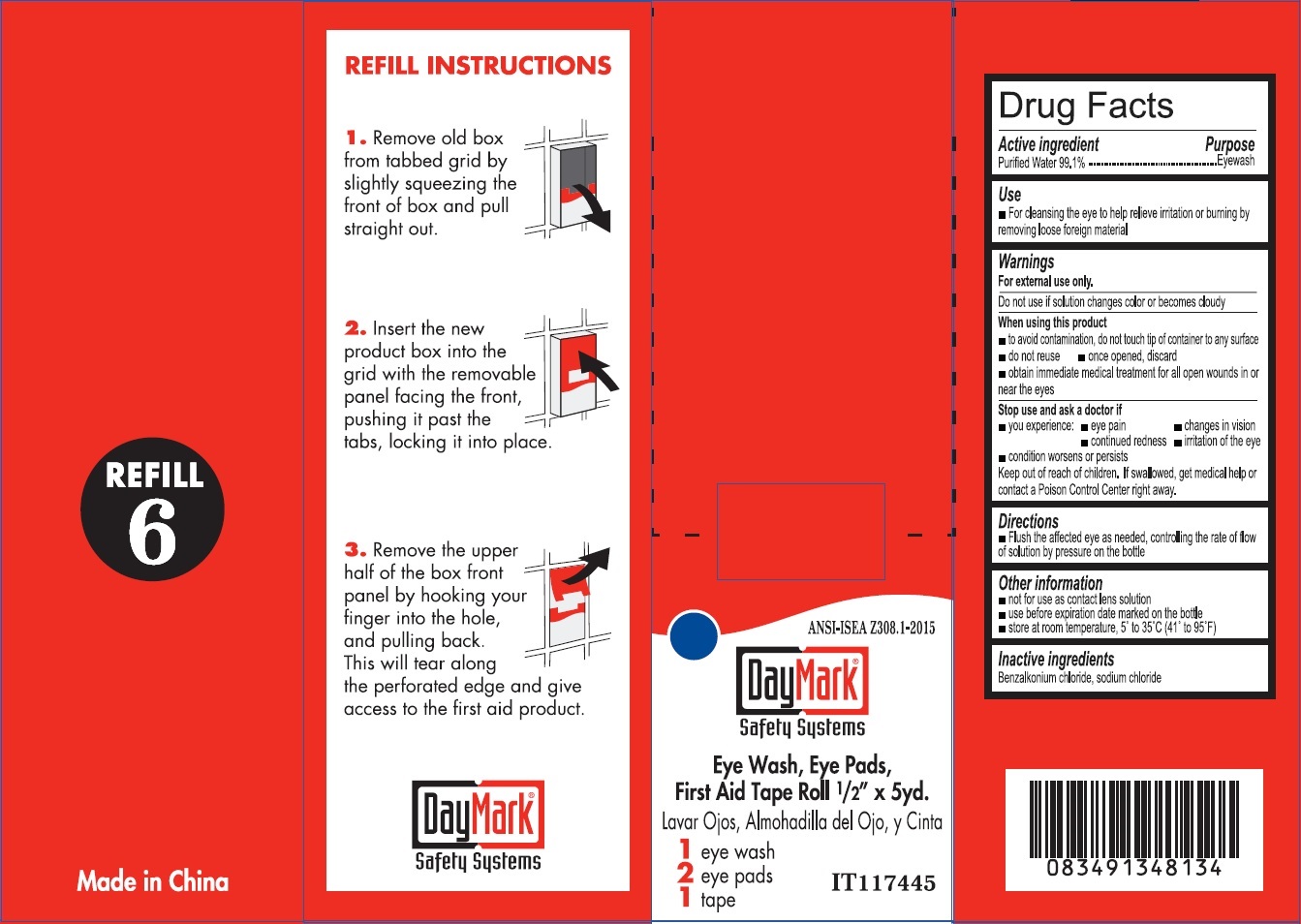 DRUG LABEL: Eye Wash
NDC: 49687-0010 | Form: SOLUTION
Manufacturer: CMC Group Inc.
Category: otc | Type: HUMAN OTC DRUG LABEL
Date: 20250402

ACTIVE INGREDIENTS: WATER 991 mg/1 mL
INACTIVE INGREDIENTS: BENZALKONIUM CHLORIDE; SODIUM CHLORIDE

Eye Wash

Active ingredient

Purified Water 99.1%

Purpose

Eyewash

Use

- For cleansing the eye to help relieve irritaion or burning by removing loose foreign material

Warnings

For external use only.

Do not use

if solution changes color or becomes cloudy

When using this product

- to avoid contamination, do not touch tip of container to any surface
- do not reuse
- once opened, discard
- obtain immediate medical treatment for all open wounds in or near the eyes

Stop use and ask a doctor if

you experience:

- eye pain
- changes in vision
- continued redness
- irritation of the eye

- condition worsens or perisists

Keep out of reach of children.

If swallowed, get medical help of contact a Poison Control Center right away.

Directions

- Flush the affected eyes as needed, controlling the rate of flow of solution by pressure on the bottle

Other information

- not for use as contact len solution
- use before expiration date marked on the bottle
- store at room temperature, 5o to 35oC (41o to 95oF)

Inactive ingredients

Benzalkonium chloride, sodium chloride